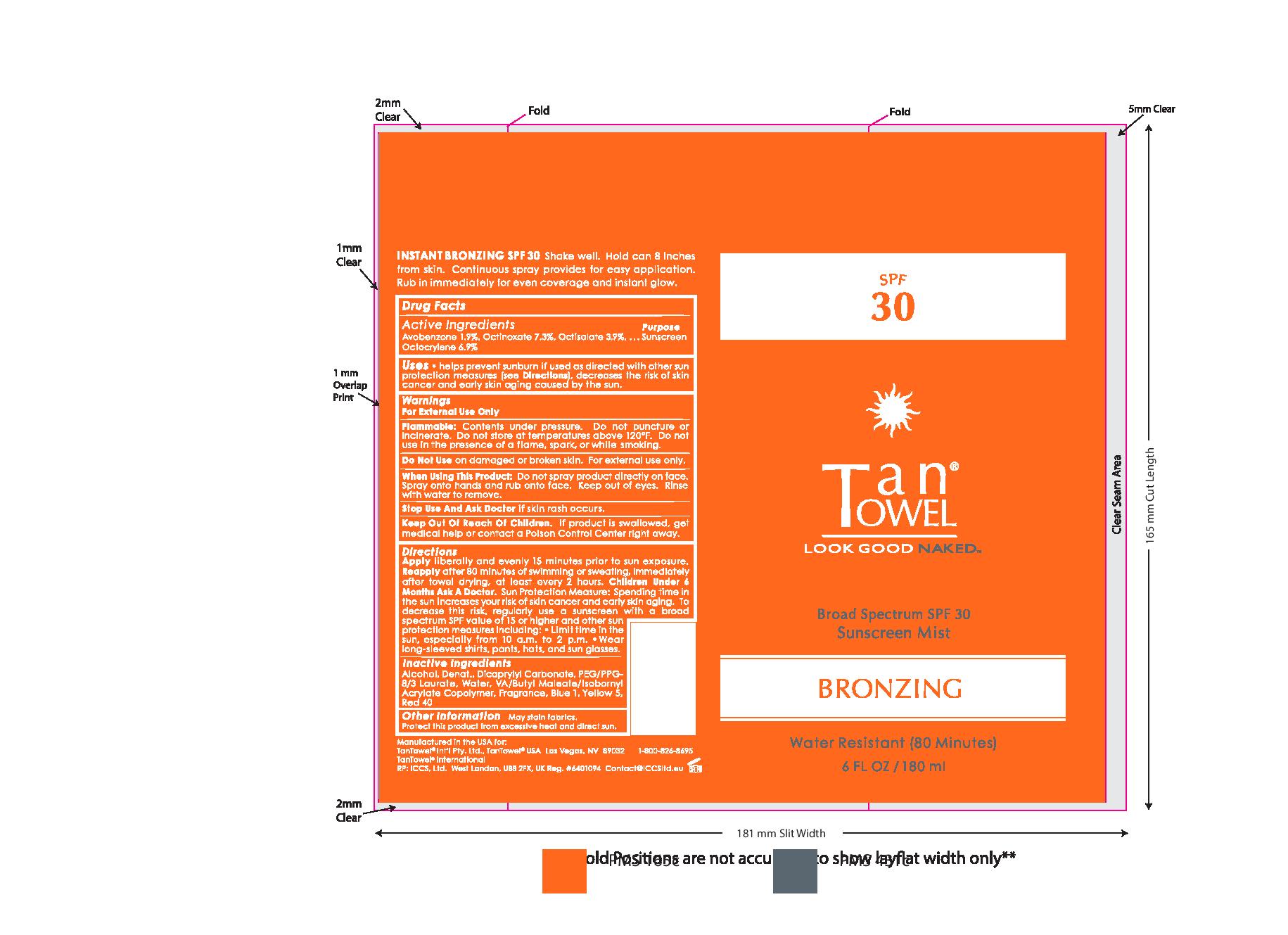 DRUG LABEL: Tan Towel SPF 30 Bronzing Mist
NDC: 76150-148 | Form: AEROSOL, SPRAY
Manufacturer: Bell International Laboratories
Category: otc | Type: HUMAN OTC DRUG LABEL
Date: 20210114

ACTIVE INGREDIENTS: AVOBENZONE 2 g/100 mL; OCTOCRYLENE 7 g/100 mL; OCTINOXATE 7.5 g/100 mL; OCTISALATE 4 g/100 mL
INACTIVE INGREDIENTS: WATER; ALCOHOL; FD&C BLUE NO. 1; DICAPRYLYL CARBONATE; FD&C YELLOW NO. 5; FD&C RED NO. 40

Tan Towel SPF 30 Bronzing Mist

Active Ingredients...Purpose

Avobenzone 1.9%, Octinoxate 7.3%, Octisalate 3.9%, Octocrylene 6.9%....Sunscreen

Uses

helps prevent sunburn if used as directed with other sun protection measures (see Directions), decreases the risk of skin cancer and early skin aging caused by the sun.

Warnings

For External Use Only

Flammable: Contents under pressure. Do not puncture or incinerate. Do not store at temperatures above 120oF. Do not use in the presence of a flame, spark, or while smoking.

Do Not Use on damaged or broken skin. For external use only.

When Using This Product: Do not spray product directly on face. Spray onto hands and rub onto face. Keep out of eyes. Rinse with water to remove.

Stop Use And Ask Doctor if skin rash occures.

Keep Out Of Reach Of Children. If product is swallowed, get medical help or contact a Poison Control Center right away.

Directions

Apply liberally and evenly 15 minutes prior to sun exposure.

Reapply after 80 minutes of swimming or sweating, immediately after towel drying, at least every 2 hours.

Children Under 6 Months Ask A Doctor.

Sun Protection Measure: Spending time in the sun increases your risk of skin cancer and early skin aging. To decrease this risk, regularly use a sunscreen with a broad spectrum SPF value of 15 or higher and other sun protection measures including:

- Limit time in the sun, especially from 10a.m. to 2 p.m.
- Wear long-sleeved shirts, pants, hats, and sun glasses.

Inactie Ingredients

Alcohol, Denat., Dicaprylyl Carbonate, PEG/PPG-8/3 Laurate, Water, VA/Butyl Maleate/Isobornyl Acrylate Copolymer, Fragrance, Blue 1, Yellow 5, Red 40

Other Information

May stain fabrics. Protect this product from excessive heat and direct sun.